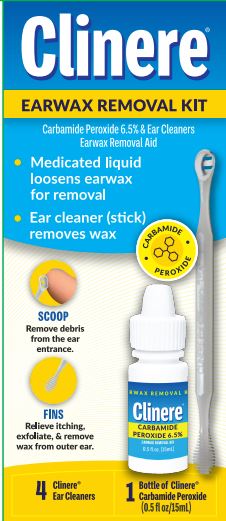 DRUG LABEL: Clinere Ear Wax Remover
NDC: 68229-102 | Form: LIQUID
Manufacturer: Quest Products
Category: otc | Type: HUMAN OTC DRUG LABEL
Date: 20260108

ACTIVE INGREDIENTS: CARBAMIDE PEROXIDE 0.065 g/1 mL
INACTIVE INGREDIENTS: CITRIC ACID MONOHYDRATE; WATER; PROPYLENE GLYCOL; SODIUM LAURYL SULFATE; SODIUM CITRATE; GLYCERIN

Clinere Ear Wax Removal Kit

Active Ingredient

Carbamide Peroxide 6.5%

Purpose

Earwax Removal Aid

Uses

For occassional use as an aid to soften, loosen and remove excess earwax.

Warnings

For use in the ear only

Ask a Doctor before use if you have

- ear drainage or discharge
- ear pain
- irritation or rash in the ear
- dizziness
- an injury or perforation (hole) of the eardrum
- recently had ear surgery

When using this product

avoid contact with the eyes.

Stop use and ask a Doctor if

- you need to use for more than four days
- excessive earwax remains after use of this product

Keep out of reach of Children.

If swallowed, get medical help or contact a Poison Control Center right away.

Directions

FOR USE IN THE EAR ONLY.

Adults and children over 12 years of age:

- tilt head sideways and place 5-10 drops into each ear canal.
- Tip of applicator should not enter ear canal.
- Keep drops in ear for several minutes by keeping head tilted or placing cotton in ear.
- Use twice daily for up to four days if needed, or as directed by a doctor.
- Any wax remaining in the ear may be removed by gently flushing the ear with warm water, using a soft rubber bulb ear syringe, or by use of the included Clinere® ear cleaning tool. (See separate directions)

Children under 12 years: Consult a doctor.

Other Information

- Store at 15° - 30°C (59° - 86°F)
- Avoid exposing bottle to excessive heat or direct sunlight
- Store bottle in the outer carton
- Keep cap on bottle when not in use
- Product foams on contact with ear wax due to release of oxygen. There may be an associated crackling sound.

Inactive Ingredients

Anhydrous Citric Acid, Glycerin, Propylene Glycol, Sodium Citrate, Sodium Lauryl Sulfate, Water

Questions?

1-800-328-5890

Weekdays 8:30am -5:00pm CST